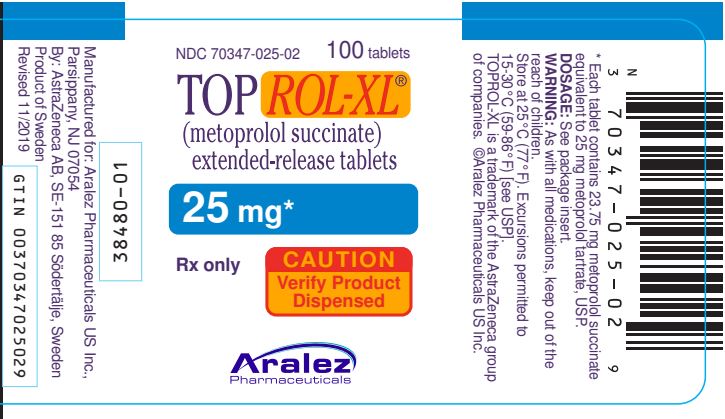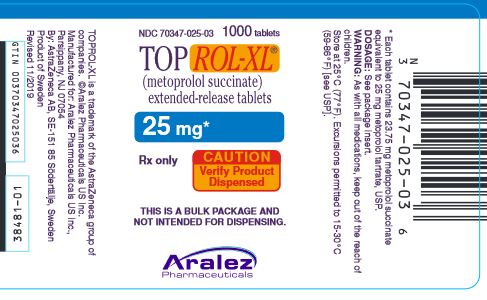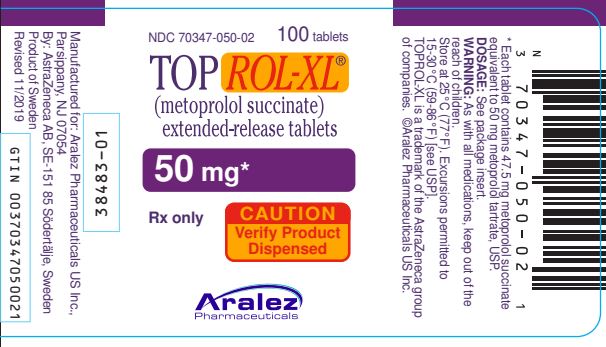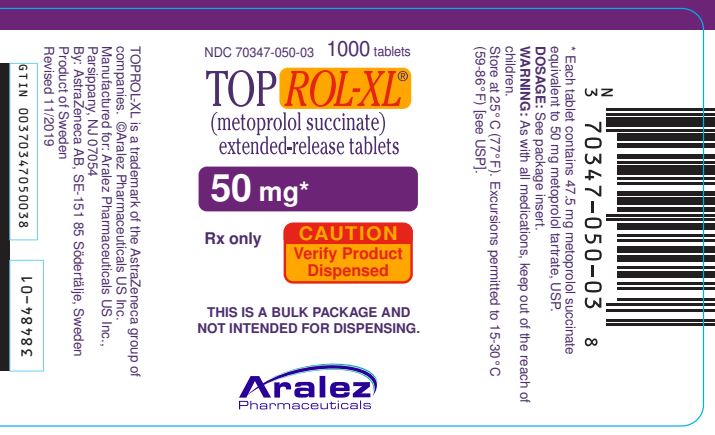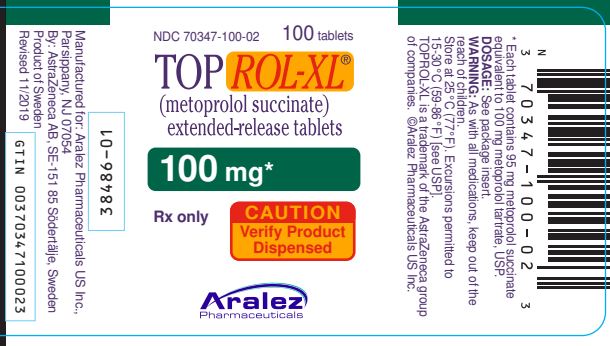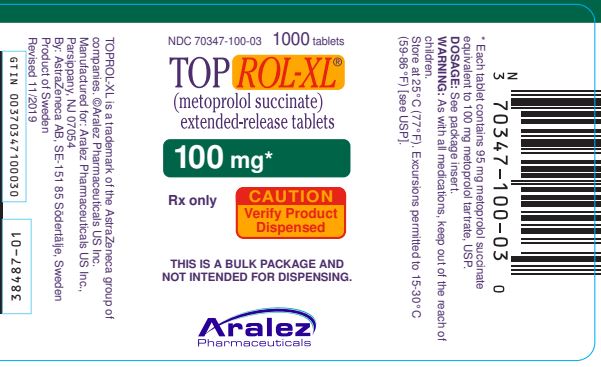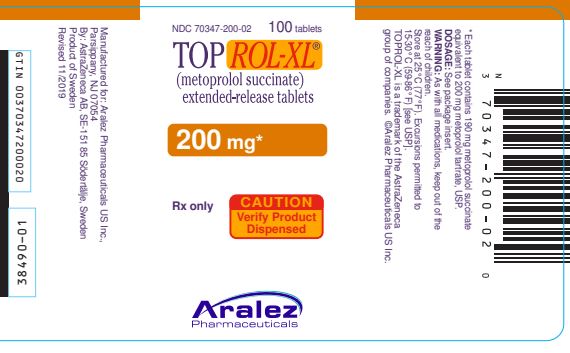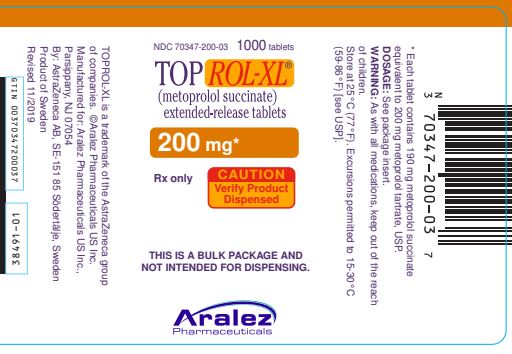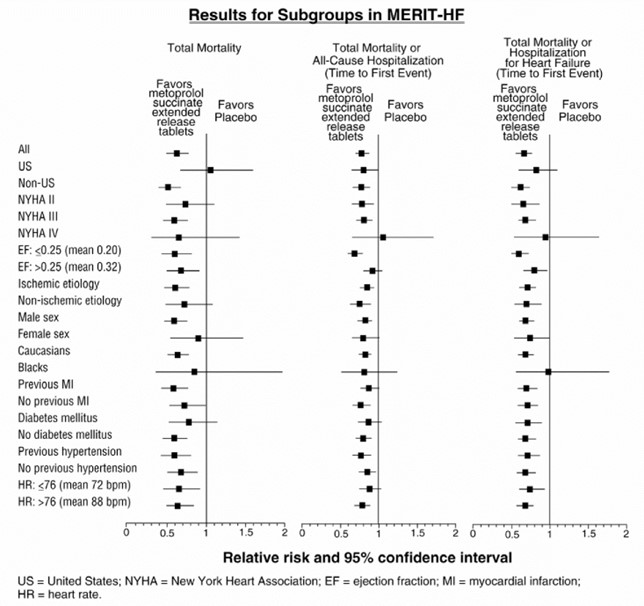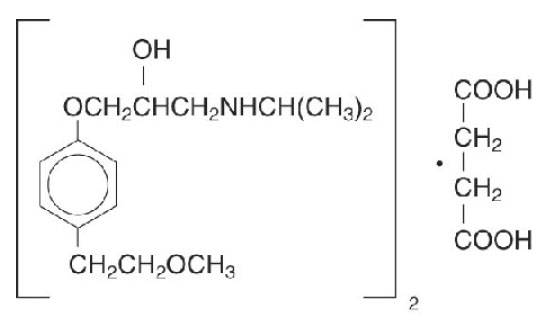 DRUG LABEL: TOPROL
NDC: 70347-025 | Form: TABLET, EXTENDED RELEASE
Manufacturer: Aralez Pharmaceuticals US Inc.
Category: prescription | Type: HUMAN PRESCRIPTION DRUG LABEL
Date: 20230424

ACTIVE INGREDIENTS: METOPROLOL SUCCINATE 25 mg/1 1
INACTIVE INGREDIENTS: SILICON DIOXIDE; SODIUM STEARYL FUMARATE; TITANIUM DIOXIDE; POLYETHYLENE GLYCOL 6000; PARAFFIN; HYPROMELLOSES

HIGHLIGHTS OF PRESCRIBING INFORMATION

These highlights do not include all the information needed to use TOPROL-XL® safely and effectively. See full prescribing information for TOPROL-XL.
TOPROL-XL® (metoprolol succinate) Tablet, Extended-Release for Oral Use
Initial U.S. Approval: 1992

1 INDICATIONS AND USAGE

TOPROL-XL, metoprolol succinate, is a beta-adrenergic blocker indicated for the treatment of:

- Hypertension, to lower blood pressure. Lowering blood pressure reduces the risk of fatal and non-fatal cardiovascular events, primarily strokes and myocardial infarctions. (1.1)
- Angina Pectoris. (1.2)
- Heart Failure, to reduce the risk of cardiovascular mortality and heart failure hospitalizations in patients with heart failure (1.3)

2 DOSAGE AND ADMINISTRATION

- Administer once daily. Titrate at weekly or longer intervals as needed and tolerated. (2)
- Hypertension: Starting dose is 25 to 100 mg. (2.1)
- Angina Pectoris: Starting dose is 100 mg. (2.2)
- Heart Failure: Starting dose is 12.5 or 25 mg. (2.3)
- Switching from immediate-release metoprolol to TOPROL-XL: use the same total daily dose of TOPROL-XL. (2)

3 DOSAGE FORMS AND STRENGTHS

•TOPROL-XL Extended-Release Tablets (metoprolol succinate): 25 mg, 50 mg, 100 mg, and 200 mg. (3)

4 CONTRAINDICATIONS

- Known hypersensitivity to product components. (4)
- Severe bradycardia: Greater than first degree heart block, or sick sinus syndrome without a pacemaker. (4)
- Cardiogenic shock or decompensated heart failure. (4)

5 WARNINGS AND PRECAUTIONS

- Abrupt cessation may exacerbate myocardial ischemia. (5.1)
- Heart Failure: Worsening cardiac failure may occur. (5.2)
- Bronchospastic Disease: Avoid beta blockers. (5.3)
- Concomitant use of glycosides, clonidine, diltiazem, and verapamil with beta-blockers can increase the risk of bradycardia. (5.4)
- Pheochromocytoma: Initiate therapy with an alpha blocker. (5.5)
- Major Surgery: Avoid initiation of high-dose extended-release metoprolol in patients undergoing non-cardiac surgery. Do not routinely withdraw chronic beta blocker therapy prior to surgery. (5.6, 6.1)
- Hypoglycemia: May increase risk for hypoglycemia and mask early warning signs. (5.7)
- Thyrotoxicosis: Abrupt withdrawal in patients with thyrotoxicosis might precipitate a thyroid storm. (5.8)
- Peripheral Vascular Disease: Can aggravate symptoms of arterial insufficiency. (5.9)
- Patients may be unresponsive to the usual doses of epinephrine used to treat allergic reaction. (5.10)

6 ADVERSE REACTIONS

- Most common adverse reactions: tiredness, dizziness, depression, shortness of breath, bradycardia, hypotension, diarrhea, pruritus, rash. (6.1)

To report SUSPECTED ADVERSE REACTIONS, contact Melinta Therapeutics at 1-844-633-6568 or FDA at 1-800-FDA-1088 or www.fda.gov/medwatch.

7 DRUG INTERACTIONS

- Catecholamine-depleting drugs may have an additive effect when given with beta-blocking agents. (7.1)
- CYP2D6 Inhibitors are likely to increase metoprolol concentration. (7.2)
- Beta-blockers including metoprolol, may exacerbate the rebound hypertension that can follow the withdrawal of clonidine. (7.3)

8 USE IN SPECIFIC POPULATIONS

- Hepatic Impairment: Consider initiating TOPROL-XL therapy at low doses and gradually increase dosage to optimize therapy, while monitoring closely for adverse events. (8.6)

FULL PRESCRIBING INFORMATION

1 INDICATIONS AND USAGE

1.1 Hypertension

TOPROL-XL is indicated for the treatment of hypertension, to lower blood pressure. Lowering blood pressure lowers the risk of fatal and non-fatal cardiovascular events, primarily strokes and myocardial infarctions. These benefits have been seen in controlled trials of antihypertensive drugs from a wide variety of pharmacologic classes including metoprolol.

Control of high blood pressure should be part of comprehensive cardiovascular risk management, including, as appropriate, lipid control, diabetes management, antithrombotic therapy, smoking cessation, exercise, and limited sodium intake. Many patients will require more than 1 drug to achieve blood pressure goals. For specific advice on goals and management, see published guidelines, such as those of the National High Blood Pressure Education Program’s Joint National Committee on Prevention, Detection, Evaluation, and Treatment of High Blood Pressure (JNC).

Numerous antihypertensive drugs, from a variety of pharmacologic classes and with different mechanisms of action, have been shown in randomized controlled trials to reduce cardiovascular morbidity and mortality, and it can be concluded that it is blood pressure reduction, and not some other pharmacologic property of the drugs, that is largely responsible for those benefits. The largest and most consistent cardiovascular outcome benefit has been a reduction in the risk of stroke, but reductions in myocardial infarction and cardiovascular mortality also have been seen regularly.

Elevated systolic or diastolic pressure causes increased cardiovascular risk, and the absolute risk increase per mmHg is greater at higher blood pressures, so that even modest reductions of severe hypertension can provide substantial benefit. Relative risk reduction from blood pressure reduction is similar across populations with varying absolute risk, so the absolute benefit is greater in patients who are at higher risk independent of their hypertension (for example, patients with diabetes or hyperlipidemia), and such patients would be expected to benefit from more aggressive treatment to a lower blood pressure goal.

Some antihypertensive drugs have smaller blood pressure effects (as monotherapy) in black patients, and many antihypertensive drugs have additional approved indications and effects (e.g., on angina, heart failure, or diabetic kidney disease). These considerations may guide selection of therapy.

TOPROL-XL may be administered with other antihypertensive agents.

1.2 Angina Pectoris

TOPROL-XL is indicated in the long-term treatment of angina pectoris, to reduce angina attacks and to improve exercise tolerance.

1.3 Heart Failure

TOPROL-XL is indicated to reduce the risk of cardiovascular mortality and heart-failure hospitalization in patients with heart failure.

2 DOSAGE AND ADMINISTRATION

2.1 Hypertension

Adults: The usual initial dosage is 25 to 100 mg daily in a single dose. Adjust dosage at weekly (or longer) intervals until optimum blood pressure reduction is achieved. In general, the maximum effect of any given dosage level will be apparent after 1 week of therapy. Dosages above 400 mg per day have not been studied.

Pediatric Hypertensive Patients ≥ 6 Years of age: The recommended starting dose of TOPROL-XL is 1 mg/kg once daily, but the maximum initial dose should not exceed 50 mg once daily. Adjust dosage according to blood pressure response. Doses above 2 mg/kg (or in excess of 200 mg) once daily have not been studied in pediatric patients [see Use in Specific Populations (8.4) and Clinical Pharmacology (12.3)].

TOPROL-XL has not been studied in pediatric patients < 6 years of age [see Use inSpecific Populations (8.4)].

2.2 Angina Pectoris

Individualize the dosage of TOPROL-XL. The usual initial dosage is 100 mg daily, given in a single dose. Gradually increase the dosage at weekly intervals until optimum clinical response has been obtained or there is a pronounced slowing of the heart rate. Dosages above 400 mg per day have not been studied. If treatment is to be discontinued, reduce the dosage gradually over a period of 1 - 2 weeks [see Warnings and Precautions (5)].

2.3 Heart Failure

Dosage must be individualized and closely monitored during up-titration. Prior to initiation of TOPROL-XL, stabilize the dose of other heart failure drug therapy. The recommended starting dose of TOPROL-XL is 25 mg once daily for two weeks in patients with NYHA Class II heart failure and 12.5 mg once daily in patients with more severe heart failure. Double the dose every two weeks to the highest dosage level tolerated by the patient or up to 200 mg of TOPROL-XL. Initial difficulty with titration should not preclude later attempts to introduce TOPROL-XL. If patients experience symptomatic bradycardia, reduce the dose of TOPROL-XL. If transient worsening of heart failure occurs, consider treating with increased doses of diuretics, lowering the dose of TOPROL-XL, or temporarily discontinuing it. The dose of TOPROL-XL should not be increased until symptoms of worsening heart failure have been stabilized.

2.4 Administration

TOPROL-XL tablets are scored and can be divided; however, do not crush or chew the whole or half tablet.

3 DOSAGE FORMS AND STRENGTHS

25 mg tablets: White, oval, biconvex, film-coated scored tablet engraved with “A/β”.

50 mg tablets: White, round, biconvex, film-coated scored tablet engraved with “A/mo”.

100 mg tablets: White, round, biconvex, film-coated scored tablet engraved with “A/ms”.

200 mg tablets: White, oval, biconvex, film-coated scored tablet engraved with “A/mY”.

4 CONTRAINDICATIONS

TOPROL-XL is contraindicated in severe bradycardia, second- or third-degree heart block, cardiogenic shock, decompensated heart failure, sick sinus syndrome (unless a permanent pacemaker is in place), and in patients who are hypersensitive to any component of this product.

5 WARNINGS AND PRECAUTIONS

5.1 Abrupt Cessation of Therapy

Following abrupt cessation of therapy with certain beta-blocking agents, exacerbations of angina pectoris and, in some cases, myocardial infarction have occurred. When discontinuing chronically administered TOPROL-XL, particularly in patients with ischemic heart disease, gradually reduce the dosage over a period of 1 to 2 weeks and monitor the patient. If angina markedly worsens or acute coronary ischemia develops, promptly reinstate TOPROL-XL, and take measures appropriate for the management of unstable angina. Warn patients not to interrupt therapy without their physician’s advice. Because coronary artery disease is common and may be unrecognized, avoid abruptly discontinuing TOPROL-XL in patients treated only for hypertension.

5.2 Heart Failure

Worsening cardiac failure may occur during up-titration of TOPROL-XL. If such symptoms occur, increase diuretics and restore clinical stability before advancing the dose of TOPROL-XL [see Dosage and Administration (2)]. It may be necessary to lower the dose of TOPROL-XL or temporarily discontinue it. Such episodes do not preclude subsequent successful titration of TOPROL-XL.

5.3 Bronchospastic Disease

Patients with bronchospastic diseases should, in general, not receive beta-blockers. Because of its relative beta1- cardioselectivity, however, TOPROL-XL may be used in patients with bronchospastic disease who do not respond to, or cannot tolerate, other antihypertensive treatment. Because beta1-selectivity is not absolute, use the lowest possible dose of TOPROL-XL. Bronchodilators, including beta2-agonists, should be readily available or administered concomitantly [see Dosage and Administration (2)].

5.4 Bradychardia

Bradycardia, including sinus pause, heart block, and cardiac arrest have occurred with the use of TOPROL-XL. Patients with first-degree atrioventricular block, sinus node dysfunction, conduction disorders (including Wolff- Parkinson-White) or on concomitant drugs that cause bradycardia [see Drug Interactions (7.3)], may be at increased risk. Monitor heart rate in patients receiving TOPROL-XL. If severe bradycardia develops, reduce or stop TOPROL-XL.

5.5 Pheochromocytoma

If TOPROL-XL is used in the setting of pheochromocytoma, it should be given in combination with an alpha-blocker, and only after the alpha-blocker has been initiated. Administration of beta-blockers alone in the setting of pheochromocytoma has been associated with a paradoxical increase in blood pressure due to the attenuation of beta-mediated vasodilatation in skeletal muscle.

5.6 Major Surgery

Avoid initiation of a high-dose regimen of extended-release metoprolol in patients undergoing non-cardiac surgery, since such use in patients with cardiovascular risk factors has been associated with bradycardia, hypotension, stroke, and death.

Chronically administered beta-blocking therapy should not be routinely withdrawn prior to major surgery; however, the impaired ability of the heart to respond to reflex adrenergic stimuli may augment the risks of general anesthesia and surgical procedures.

5.7 Hypoglycemia

Beta-blockers may prevent early warning signs of hypoglycemia, such as tachycardia, and increase the risk for severe or prolonged hypoglycemia at any time during treatment, especially in patients with diabetes mellitus or children and patients who are fasting (i.e., surgery, not eating regularly, or are vomiting). If severe hypoglycemia occurs, patients should be instructed to seek emergency treatment.

5.8 Thyrotoxicosis

Beta-adrenergic blockade may mask certain clinical signs of hyperthyroidism, such as tachycardia. Abrupt withdrawal of beta-blockade may precipitate a thyroid storm.

5.9 Peripheral Vascular Disease

Beta-blockers can precipitate or aggravate symptoms of arterial insufficiency in patients with peripheral vascular disease.

5.10 Anaphylactic Reaction

While taking beta-blockers, patients with a history of severe anaphylactic reactions to a variety of allergens may be more reactive to repeated challenge and may be unresponsive to the usual doses of epinephrine used to treat an allergic reaction.

6 ADVERSE REACTIONS

The following adverse reactions are described elsewhere in labeling:

- Worsening angina or myocardial infarction [see Warnings and Precautions (5)].
- Worsening heart failure [see Warnings and Precautions (5)].
- Worsening AV block [see Contraindications (4)].

6.1 Clinical Trials Experience

Because clinical trials are conducted under widely varying conditions, adverse reaction rates observed in the clinical trials of a drug cannot be directly compared to rates in the clinical trials of another drug and may not reflect the rates observed in practice. The adverse reaction information from clinical trials does, however, provide a basis for identifying the adverse events that appear to be related to drug use and for approximating rates.

Hypertension and Angina: Most adverse reactions have been mild and transient. The most common (>2%) adverse reactions are tiredness, dizziness, depression, diarrhea, shortness of breath, bradycardia, and rash.

Heart Failure: In the MERIT-HF study comparing TOPROL-XL in daily doses up to 200 mg (mean dose 159 mg once-daily; n=1990) to placebo (n=2001), 10.3% of TOPROL-XL patients discontinued for adverse reactions vs. 12.2% of placebo patients.

The table below lists adverse reactions in the MERIT-HF study that occurred at an incidence of ≥ 1% in the TOPROL-XL group and greater than placebo by more than 0.5%, regardless of the assessment of causality.

Adverse Reactions Occurring in the MERIT-HF Study at an Incidence ≥1% in the TOPROL-XL Group and Greater Than Placebo by More Than 0.5%
 | TOPROL-XL; n=1990 % of patients | Placebo; n=2001 % of patients
Dizziness/vertigo | 1.8 | 1.0
Bradycardia | 1.5 | 0.4

Post-operative Adverse Events: In a randomized, double-blind, placebo-controlled trial of 8351 patients with or at risk for atherosclerotic disease undergoing non-vascular surgery and who were not taking beta–blocker therapy, TOPROL-XL 100 mg was started 2 to 4 hours prior to surgery then continued for 30 days at 200 mg per day. TOPROL-XL use was associated with a higher incidence of bradycardia (6.6% vs. 2.4%; HR, 2.74; 95% CI 2.19, 3.43), hypotension (15% vs. 9.7%; HR 1.55; 95% CI 1.37, 1.74), stroke (1.0% vs. 0.5%; HR 2.17; 95% CI 1.26, 3.74) and death (3.1% vs. 2.3%; HR 1.33; 95% CI 1.03, 1.74) compared to placebo.

6.2 Post-Marketing Experience

The following adverse reactions have been identified during post-approval use of TOPROL-XL or immediate-release metoprolol. Because these reactions are reported voluntarily from a population of uncertain size, it is not always possible to reliably estimate their frequency or establish a causal relationship to drug exposure.

Cardiovascular: Cold extremities, arterial insufficiency (usually of the Raynaud type), palpitations, peripheral edema, syncope, chest pain, hypotension.

Respiratory: Wheezing (bronchospasm), dyspnea.

Central Nervous System: Confusion, short-term memory loss, headache, somnolence, nightmares, insomnia, anxiety/nervousness, hallucinations, paresthesia.

Gastrointestinal: Nausea, dry mouth, constipation, flatulence, heartburn, hepatitis, vomiting.

Hypersensitive Reactions: Pruritus.

Miscellaneous: Musculoskeletal pain, arthralgia, blurred vision, decreased libido, male impotence, tinnitus, reversible alopecia, agranulocytosis, dry eyes, worsening of psoriasis, Peyronie’s disease, sweating, photosensitivity, taste disturbance.

Potential Adverse Reactions: In addition, there are adverse reactions not listed above that have been reported with other beta-adrenergic blocking agents and should be considered potential adverse reactions to TOPROL-XL.

Central Nervous System: Reversible mental depression progressing to catatonia; an acute reversible syndrome characterized by disorientation for time and place, short-term memory loss, emotional lability, clouded sensorium, and decreased performance on neuropsychometrics.

Hematologic: Agranulocytosis, nonthrombocytopenic purpura, thrombocytopenic purpura.

Hypersensitive Reactions: Laryngospasm, respiratory distress.

7 DRUG INTERACTIONS

7.1 Catecholamine Depleting Drugs

Catecholamine depleting drugs (e.g., reserpine, monoamine oxidase (MAO) inhibitors) may have an additive effect when given with beta-blocking agents. Observe patients treated with TOPROL-XL plus a catecholamine depletor for evidence of hypotension or marked bradycardia, which may produce vertigo, syncope, or postural hypotension.

7.2 CYP2D6 Inhibitors

Drugs that are strong inhibitors of CYP2D6 such as quinidine, fluoxetine, paroxetine, and propafenone were shown to double metoprolol concentrations. While there is no information about moderate or weak inhibitors, these too are likely to increase metoprolol concentration. Increases in plasma concentration decrease the cardioselectivity of metoprolol [see Clinical Pharmacology (12.3)]. Monitor patients closely when the combination cannot be avoided.

7.3 Digitalis, Clonidine, and Calcium Channel Blockers

Digitalis glycosides, clonidine, diltiazem, and verapamil slow atrioventricular conduction and decrease heart rate. Concomitant use with beta-blockers can increase the risk of bradycardia.

If clonidine and a beta-blocker, such as metoprolol, are co-administered, withdraw the beta-blocker several days before the gradual withdrawal of clonidine because beta-blockers may exacerbate the rebound hypertension that can follow the withdrawal of clonidine. If replacing clonidine by beta-blocker therapy, delay the introduction of beta-blockers for several days after clonidine administration has stopped.

8 USE IN SPECIFIC POPULATIONS

8.1 Pregnancy

Risk Summary

Untreated hypertension and heart failure during pregnancy can lead to adverse outcomes for the mother and the fetus (see Clinical Considerations). Available data from published observational studies have not demonstrated a drug-associated risk of major birth defects, miscarriage, or adverse maternal or fetal outcomes with metoprolol use during pregnancy. However, there are inconsistent reports of intrauterine growth restriction, preterm birth, and perinatal mortality with maternal use of beta-blockers, including metoprolol, during pregnancy (see Data). In animal reproduction studies, metoprolol has been shown to increase post-implantation loss and decrease neonatal survival in rats at oral dosages of 500 mg/kg/day, approximately 24 times the daily dose of 200 mg in a 60-kg patient on a mg/m^2 basis.

The estimated background risk of major birth defects and miscarriage for the indicated population is unknown. All pregnancies have a background risk of birth defect, loss, or other adverse outcomes. In the U.S. general population, the estimated background risk of major birth defects and miscarriage in clinically recognized pregnancies is 2 to 4% and 15 to 20%, respectively.

Clinical consideration

Disease-associated maternal and/or embryo/fetal risk

Hypertension in pregnancy increases the maternal risk for pre-eclampsia, gestational diabetes, premature delivery, and delivery complications (e.g., need for cesarean section, and post-partum hemorrhage). Hypertension increases the fetal risk for intrauterine growth restriction and intrauterine death. Pregnant women with hypertension should be carefully monitored and managed accordingly.

Stroke volume and heart rate increase during pregnancy, increasing cardiac output, especially during the first trimester. There is a risk for preterm birth with pregnant women with chronic heart failure in 3rd trimester of pregnancy.

Fetal/Neonatal adverse reactions

Metoprolol crosses the placenta. Neonates born to mothers who are receiving metoprolol during pregnancy, may be at risk for hypotension, hypoglycemia, bradycardia, and respiratory depression. Observe neonates and manage accordingly.

Data

Human Data

Data from published observational studies did not demonstrate an association of major congenital malformations and use of metoprolol in pregnancy. The published literature has reported inconsistent findings of intrauterine growth retardation, preterm birth, and perinatal mortality with maternal use of metoprolol during pregnancy; however, these studies have methodological limitations hindering interpretation. Methodological limitations include retrospective design, concomitant use of other medications, and other unadjusted confounders that may account for the study findings including the underlying disease in the mother. These observational studies cannot definitively establish or exclude any drug-associated risk during pregnancy.

Animal Data

Metoprolol has been shown to increase post-implantation loss and decrease neonatal survival in rats at oral dosages of 500 mg/kg/day, i.e., 24 times, on a mg/m^2 basis, the daily dose of 200 mg in a 60-kg patient.

No fetal abnormalities were observed when pregnant rats received metoprolol orally up to a dose of 200 mg/kg/day, i.e., 10 times, the daily dose of 200 mg in a 60-kg patient.

8.2 Lactation

Risk Summary

Limited available data from published literature report that metoprolol is present in human milk. The estimated daily infant dose of metoprolol received from breastmilk ranges from 0.05 mg to less than 1 mg. The estimated relative infant dosage was 0.5% to 2% of the mother's weight-adjusted dosage (see Data). No adverse reactions of metoprolol on the breastfed infant have been identified. There is no information regarding the effects of metoprolol on milk production.

Clinical consideration

Monitoring for adverse reactions

Monitor the breastfed infant for bradycardia and other symptoms of beta-blockade such as listlessness (hypoglycemia).

Data

Based on published case reports, the estimated infant daily dose of metoprolol received from breast milk range from 0.05 mg to less than 1 mg. The estimated relative infant dosage was 0.5% to 2% of the mother’s weight-adjusted dosage.

In two women who were taking unspecified amount of metoprolol, milk samples were taken after one dose of metoprolol. The estimated amount of metoprolol and alpha-hydroxy metoprolol in breast milk is reported to be less than 2% of the mother's weight-adjusted dosage.

In a small study, breast milk was collected every 2 to 3 hours over one dosage interval, in three mothers (at least 3 months postpartum) who took metoprolol of unspecified amount. The average amount of metoprolol present in breast milk was 71.5 mcg/day (range 17.0 to 158.7). The average relative infant dosage was 0.5% of the mother's weight-adjusted dosage.

8.3 Females and Males of Reproductive Potential

Risk Summary

Based on the published literature, beta-blockers (including metoprolol) may cause erectile dysfunction and inhibit sperm motility.

No evidence of impaired fertility due to metoprolol was observed in rats [see Nonclinical Toxicology (13.1)].

8.4 Pediatric Use

One hundred forty-four hypertensive pediatric patients aged 6 to 16 years were randomized to placebo or to one of three dose levels of TOPROL-XL (0.2, 1, or 2 mg/kg once daily) and followed for 4 weeks. The study did not meet its primary endpoint (dose response for reduction in SBP). Some pre-specified secondary endpoints demonstrated effectiveness including:

- Dose-response for reduction in DBP,
- 1 mg/kg vs. placebo for change in SBP, and
- 2 mg/kg vs. placebo for change in SBP and DBP.

The mean placebo corrected reductions in SBP ranged from 3 to 6 mmHg, and DBP from 1 to 5 mmHg. Mean reduction in heart rate ranged from 5 to 7 bpm but considerably greater reductions were seen in some individuals [see Dosage and Administration (2.1)].

No clinically relevant differences in the adverse event profile were observed for pediatric patients aged 6 to 16 years as compared with adult patients.

Safety and effectiveness of TOPROL-XL have not been established in patients < 6 years of age.

8.5 Geriatric Use

Clinical studies of TOPROL-XL in hypertension did not include sufficient numbers of subjects aged 65 and over to determine whether they respond differently from younger subjects. Other reported clinical experience in hypertensive patients has not identified differences in responses between elderly and younger patients.

Of the 1,990 patients with heart failure randomized to TOPROL-XL in the MERIT-HF trial, 50% (990) were 65 years of age and older and 12% (238) were 75 years of age and older. There were no notable differences in efficacy or the rate of adverse reactions between older and younger patients.

In general, use a low initial starting dose in elderly patients given their greater frequency of decreased hepatic, renal, or cardiac function, and of concomitant disease or other drug therapy.

8.6 Hepatic Impairment

No studies have been performed with TOPROL-XL in patients with hepatic impairment. Because TOPROL-XL is metabolized by the liver, metoprolol blood levels are likely to increase substantially with poor hepatic function. Therefore, initiate therapy at doses lower than those recommended for a given indication; and increase doses gradually in patients with impaired hepatic function.

8.7 Renal Impairment

The systemic availability and half-life of metoprolol in patients with renal failure do not differ to a clinically significant degree from those in normal subjects. No reduction in dosage is needed in patients with chronic renal failure [see Clinical Pharmacology (12.3)].

10 OVERDOSAGE

Signs and Symptoms - Overdosage of TOPROL-XL may lead to severe bradycardia, hypotension, and cardiogenic shock. Clinical presentation can also include atrioventricular block, heart failure, bronchospasm, hypoxia, impairment of consciousness/coma, nausea, and vomiting.

Treatment – Consider treating the patient with intensive care. Patients with myocardial infarction or heart failure may be prone to significant hemodynamic instability. Beta-blocker overdose may result in significant resistance to resuscitation with adrenergic agents, including beta-agonists. On the basis of the pharmacologic actions of metoprolol, employ the following measures:

Hemodialysis is unlikely to make a useful contribution to metoprolol elimination [see Clinical Pharmacology (12.3)].
Bradycardia: Evaluate the need for atropine, adrenergic-stimulating drugs, or pacemaker to treat bradycardia and conduction disorders.

Hypotension: Treat underlying bradycardia. Consider intravenous vasopressor infusion, such as dopamine or norepinephrine.

Heart failure and shock: May be treated when appropriate with suitable volume expansion, injection of glucagon (if necessary, followed by an intravenous infusion of glucagon), intravenous administration of adrenergic drugs such as dobutamine, with α1 receptor agonistic drugs added in presence of vasodilation.

Bronchospasm: Can usually be reversed by bronchodilators.

11 DESCRIPTION

TOPROL-XL, metoprolol succinate, is a beta1-selective (cardioselective) adrenoceptor blocking agent, for oral administration, available as extended-release tablets. TOPROL-XL has been formulated to provide a controlled and predictable release of metoprolol for once-daily administration. The tablets comprise a multiple unit system containing metoprolol succinate in a multitude of controlled release pellets. Each pellet acts as a separate drug delivery unit and is designed to deliver metoprolol continuously over the dosage interval. The tablets contain 23.75, 47.5, 95 and 190 mg of metoprolol succinate equivalent to 25, 50, 100 and 200 mg of metoprolol tartrate, USP, respectively. Its chemical name is (±)1- (isopropyl amino)-3-[p-(2-methoxyethyl) phenoxy]-2-propanol succinate (2:1) (salt). Its structural formula is:

Metoprolol succinate, USP is a white crystalline powder with a molecular weight of 652.8. It is freely soluble in water; soluble in methanol; sparingly soluble in ethanol; slightly soluble in dichloromethane and 2-propanol; practically insoluble in ethyl acetate, acetone, diethyl ether and heptane. Inactive ingredients: silicon dioxide, cellulose compounds, sodium stearyl fumarate, polyethylene glycol, titanium dioxide, paraffin.

12 CLINICAL PHARMACOLOGY

12.1 Mechanism of Action

Metoprolol is a beta1-selective (cardioselective) adrenergic receptor blocking agent. This preferential effect is not absolute, however, and at higher plasma concentrations, metoprolol also inhibits beta2-adrenoreceptors, chiefly located in the bronchial and vascular musculature.

Metoprolol has no intrinsic sympathomimetic activity, and membrane-stabilizing activity is detectable only at plasma concentrations much greater than required for beta-blockade. Animal and human experiments indicate that metoprolol slows the sinus rate and decreases AV nodal conduction.

The relative beta1-selectivity of metoprolol has been confirmed by the following: (1) In normal subjects, metoprolol is unable to reverse the beta2-mediated vasodilating effects of epinephrine. This contrasts with the effect of nonselective beta-blockers, which completely reverse the vasodilating effects of epinephrine. (2) In asthmatic patients, metoprolol reduces FEV1 and FVC significantly less than a nonselective beta-blocker, propranolol, at equivalent beta1-receptor blocking doses.

Hypertension: The mechanism of the antihypertensive effects of beta-blocking agents has not been elucidated. However, several possible mechanisms have been proposed: (1) competitive antagonism of catecholamines at peripheral (especially cardiac) adrenergic neuron sites, leading to decreased cardiac output; (2) a central effect leading to reduced sympathetic outflow to the periphery; and (3) suppression of renin activity.

Angina Pectoris: By blocking catecholamine-induced increases in heart rate, in velocity and extent of myocardial contraction, and in blood pressure, metoprolol reduces the oxygen requirements of the heart at any given level of effort, thus making it useful in the long-term management of angina pectoris.

Heart Failure: The precise mechanism for the beneficial effects of beta-blockers in heart failure has not been elucidated.

12.2 Pharmacodynamics

Clinical pharmacology studies have confirmed the beta-blocking activity of metoprolol in man, as shown by (1) reduction in heart rate and cardiac output at rest and upon exercise, (2) reduction of systolic blood pressure upon exercise, (3) inhibition of isoproterenol-induced tachycardia, and (4) reduction of reflex orthostatic tachycardia.

The relationship between plasma metoprolol levels and reduction in exercise heart rate is independent of the pharmaceutical formulation. Beta1-blocking effects in the range of 30-80% of the maximal effect (approximately 8 to 23% reduction in exercise heart rate) correspond to metoprolol plasma concentrations from 30 to 540 nmol/L. The relative beta1-selectivity of metoprolol diminishes and blockade of beta2-adrenoceptors increases at plasma concentration above 300 nmol/L.

In five controlled studies in normal healthy subjects, extended-release metoprolol succinate administered once a day, and immediate-release metoprolol administered once to four times a day, provided comparable total beta1-blockade over 24 hours (area under the beta1-blockade versus time curve) in the dose range 100 to 400 mg. In another controlled study, 50 mg once daily for each product, extended-release metoprolol succinate produced significantly higher total beta1-blockade over 24 hours than immediate-release metoprolol. For extended-release metoprolol succinate, the percent reduction in exercise heart rate was relatively stable throughout the entire dosage interval and the level of beta1-blockade increased with increasing doses from 50 to 300 mg daily.

A controlled cross-over study in heart failure patients compared the plasma concentrations and beta1-blocking effects of 50 mg immediate-release metoprolol administered t.i.d., and 100 mg and 200 mg extended-release metoprolol succinate once daily. Extended-release metoprolol succinate 200 mg once daily produced a larger effect on suppression of exercise-induced and Holter-monitored heart rate over 24 hours compared to 50 mg t.i.d. of immediate-release metoprolol.

In other studies, treatment with metoprolol succinate produced an improvement in left ventricular ejection fraction. Metoprolol succinate was also shown to delay the increase in left ventricular end-systolic and end-diastolic volumes after 6 months of treatment.

Although beta-adrenergic receptor blockade is useful in the treatment of angina, hypertension, and heart failure there are situations in which sympathetic stimulation is vital. In patients with severely damaged hearts, adequate ventricular function may depend on sympathetic drive. In the presence of AV block, beta-blockade may prevent the necessary facilitating effect of sympathetic activity on conduction. Beta2-adrenergic blockade results in passive bronchial constriction by interfering with endogenous adrenergic bronchodilator activity in patients subject to bronchospasm and may also interfere with exogenous bronchodilators in such patients.

12.3 Pharmacokinetics

Absorption

The peak plasma levels following once-daily administration of TOPROL-XL average one-fourth to one-half the peak plasma levels obtained following a corresponding dose of conventional metoprolol, administered once daily or in divided doses. At steady state the average bioavailability of metoprolol following administration of TOPROL-XL, across the dosage range of 50 to 400 mg once daily, was 77% relative to the corresponding single or divided doses of conventional metoprolol.

The bioavailability of metoprolol shows a dose-related, although not directly proportional, increase with dose and is not significantly affected by food following TOPROL-XL administration.

The peak plasma levels following oral administration of conventional metoprolol tablets, however, approximate 50% of levels following intravenous administration, indicating about 50% first-pass metabolism.

Distribution

Metoprolol crosses the blood-brain barrier and has been reported in the CSF in a concentration 78% of the simultaneous plasma concentration. Only a small fraction of the drug (about 12%) is bound to human serum albumin.

Metabolism

Metoprolol is a racemic mixture of R- and S- enantiomers and is primarily metabolized by CYP2D6. When administered orally, it exhibits stereoselective metabolism that is dependent on oxidation phenotype.

Elimination

Elimination is mainly by biotransformation in the liver, and the plasma half-life ranges from approximately 3 to 7 hours. Less than 5% of an oral dose of metoprolol is recovered unchanged in the urine; the rest is excreted by the kidneys as metabolites that appear to have no beta-blocking activity.

Following intravenous administration of metoprolol, the urinary recovery of unchanged drug is approximately 10%.

Specific Populations

Patients with Renal Impairment

The systemic availability and half-life of metoprolol in patients with renal failure do not differ to a clinically significant degree from those in normal subjects.

Pediatric Patients

The pharmacokinetic profile of TOPROL-XL was studied in 120 pediatric hypertensive patients (6-17 years of age) receiving doses ranging from 12.5 to 200 mg once daily. The pharmacokinetics of metoprolol were similar to those described previously in adults. Metoprolol pharmacokinetics have not been investigated in patients < 6 years of age.

Body Weight, Age, and Race

Metoprolol apparent oral clearance (CL/F) increased linearly with body weight. Age, gender, and race had no significant effects on metoprolol pharmacokinetics.

Drug Interactions

CYP2D6

Metoprolol is metabolized predominantly by CYP2D6. In healthy subjects with CYP2D6 extensive metabolizer phenotype, coadministration of quinidine 100 mg, a potent CYP2D6 inhibitor, and immediate-release metoprolol 200 mg tripled the concentration of S-metoprolol and doubled the metoprolol elimination half-life. In four patients with cardiovascular disease, coadministration of propafenone 150 mg t.i.d. with immediate-release metoprolol 50 mg t.i.d. resulted in steady-state concentration of metoprolol 2- to 5-fold what is seen with metoprolol alone. Extensive metabolizers who concomitantly use CYP2D6 inhibiting drugs will have increased (several-fold) metoprolol blood levels, decreasing metoprolol's cardioselectivity [see Drug Interactions (7.2)].

12.5 Pharmacogenomics

CYP2D6 is absent in about 8% of Caucasians (poor metabolizers) and about 2% of most other populations. CYP2D6 can be inhibited by several drugs. Poor metabolizers of CYP2D6 will have increased (several-fold) metoprolol blood levels, decreasing metoprolol's cardioselectivity.

13 NONCLINICAL TOXICOLOGY

13.1 Carcinogenesis, Mutagenesis, Impairment of Fertility

Long-term studies in animals have been conducted to evaluate the carcinogenic potential of metoprolol tartrate. In 2-year studies in rats at three oral dosage levels of up to 800 mg/kg/day (41 times, on a mg/m^2 basis, the daily dose of 200 mg for a 60-kg patient), there was no increase in the development of spontaneously occurring benign or malignant neoplasms of any type. The only histologic changes that appeared to be drug related were an increased incidence of generally mild focal accumulation of foamy macrophages in pulmonary alveoli and a slight increase in biliary hyperplasia. In a 21-month study in Swiss albino mice at three oral dosage levels of up to 750 mg/kg/day (18 times, on a mg/m^2 basis, the daily dose of 200 mg for a 60-kg patient), benign lung tumors (small adenomas) occurred more frequently in female mice receiving the highest dose than in untreated control animals. There was no increase in malignant or total (benign plus malignant) lung tumors, nor in the overall incidence of tumors or malignant tumors. This 21-month study was repeated in CD-1 mice, and no statistically or biologically significant differences were observed between treated and control mice of either sex for any type of tumor.

All genotoxicity tests performed on metoprolol tartrate (a dominant lethal study in mice, chromosome studies in somatic cells, a Salmonella/mammalian-microsome mutagenicity test, and a nucleus anomaly test in somatic interphase nuclei) and metoprolol succinate (a Salmonella/mammalian-microsome mutagenicity test) were negative.

No evidence of impaired fertility due to metoprolol tartrate was observed in a study performed in rats at doses up to 22 times, on a mg/m^2 basis, the daily dose of 200 mg in a 60-kg patient.

14 CLINICAL STUDIES

14.1 Hypertension

In a double-blind study, 1092 patients with mild-to-moderate hypertension were randomized to once daily TOPROL-XL (25, 100, or 400 mg), PLENDIL® (felodipine extended-release tablets), the combination, or placebo. After 9 weeks, TOPROL-XL alone decreased sitting blood pressure by 6-8/4-7 mmHg (placebo-corrected change from baseline) at 24 hours post-dose. The combination of TOPROL-XL with PLENDIL® has greater effects on blood pressure.

In controlled clinical studies, an immediate-release dosage form of metoprolol was an effective antihypertensive agent when used alone or as concomitant therapy with thiazide-type diuretics at dosages of 100-450 mg daily. TOPROL-XL, in dosages of 100 to 400 mg once daily, produces similar β1-blockade as conventional metoprolol tablets administered two to four times daily. In addition, TOPROL-XL administered at a dose of 50 mg once daily lowered blood pressure 24-hours post-dosing in placebo-controlled studies. In controlled, comparative, clinical studies, immediate-release metoprolol appeared comparable as an antihypertensive agent to propranolol, methyldopa, and thiazide-type diuretics, and affected both supine and standing blood pressure. Because of variable plasma levels attained with a given dose and lack of a consistent relationship of antihypertensive activity to drug plasma concentration, selection of proper dosage requires individual titration.

14.2 Angina Pectoris

In controlled clinical trials, an immediate-release formulation of metoprolol has been shown to be an effective antianginal agent, reducing the number of angina attacks and increasing exercise tolerance. The dosage used in these studies ranged from 100 to 400 mg daily. TOPROL-XL, in dosages of 100 to 400 mg once daily, has been shown to possess beta-blockade similar to conventional metoprolol tablets administered two to four times daily.

14.3 Heart Failure

MERIT-HF was a randomized double-blind, placebo-controlled study of TOPROL-XL in which 3991 patients with ejection fraction ≤0.40 and NYHA Class II-IV heart failure attributable to ischemia, hypertension, or cardiomyopathy were randomized 1:1 to TOPROL-XL or placebo. The protocol excluded patients with contraindications to beta-blocker use, those expected to undergo heart surgery, and those within 28 days of myocardial infarction or unstable angina. The primary endpoints of the trial were (1) all-cause mortality plus all-cause hospitalization (time to first event) and (2) all-cause mortality. Patients were stabilized on optimal concomitant therapy for heart failure, including diuretics, ACE inhibitors, cardiac glycosides, and nitrates. At randomization, 41% of patients were NYHA Class II; 55% NYHA Class III; 65% of patients had heart failure attributed to ischemic heart disease; 44% had a history of hypertension; 25% had diabetes mellitus; 48% had a history of myocardial infarction. Among patients in the trial, 90% were on diuretics, 89% were on ACE inhibitors, 64% were on digitalis, 27% were on a lipid-lowering agent, 37% were on an oral anticoagulant, and the mean ejection fraction was 0.28. The mean duration of follow-up was one year. At the end of the study, the mean daily dose of TOPROL-XL was 159 mg.

The trial was terminated early for a statistically significant reduction in all-cause mortality (34%, nominal p= 0.00009). The risk of all-cause mortality plus all-cause hospitalization was reduced by 19% (p= 0.00012). The trial also showed improvements in heart failure-related mortality and heart failure-related hospitalizations, and NYHA functional class.

The table below shows the principal results for the overall study population. The figure below illustrates principal results for a wide variety of subgroup comparisons, including US vs. non-US populations (the latter of which was not pre-specified). The combined endpoints of all-cause mortality plus all-cause hospitalization and of mortality plus heart failure hospitalization showed consistent effects in the overall study population and the subgroups. Nonetheless, subgroup analyses can be difficult to interpret and it is not known whether these represent true differences or chance effects.

Clinical Endpoints in the MERIT-HF Study
Clinical Endpoint | Number of Patients |  | Relative Risk; (95% Cl) | Risk Reduction With TOPROL-XL | Nominal P-value
 | Placebo; n=2001 | TOPROL-XL; n=1990
All-cause mortality plus all-caused hospitalization^1 | 767 | 641 | 0.81(0.73- 0.90) | 19% | 0.00012
All-cause mortality | 217 | 145 | 0.66(0.53- 0.81) | 34% | 0.00009
All-cause mortality plus heart failure hospitalization^1 | 439 | 311 | 0.69(0.60- 0.80) | 31% | 0.0000008
Cardiovascular mortality | 203 | 128 | 0.62(0.50- 0.78) | 38% | 0.000022
Sudden death | 132 | 79 | 0.59(0.45- 0.78) | 41% | 0.0002
Death due to worsening heart failure | 58 | 30 | 0.51(0.33- 0.79) | 49% | 0.0023
Hospitalizations due to worsening heart failure^2 | 451 | 317 | N/A | N/A | 0.0000076
Cardiovascular hospitalization^2 | 773 | 649 | N/A | N/A | 0.00028

^1Time to first event
^2Comparison of treatment groups examines the number of hospitalizations (Wilcoxon test); relative risk and risk reduction are not applicable.

16 HOW SUPPLIED/STORAGE AND HANDLING

Tablets containing metoprolol succinate equivalent to the indicated weight of metoprolol tartrate, USP, are white, biconvex, film-coated, and scored.

Tablet | Shape | Engraving | Bottle of 100; NDC 70347- | Bottle of 1000; NDC 70347-
25 mg | Oval | A/β | 025-02 | 025-03
50 mg | Round | A/mo | 050-02 | 050-03
100 mg | Round | A/ms | 100-02 | 100-03
200 mg | Oval | A/mY | 200-02 | 200-03

Store at 25°C (77°F). Excursions permitted to 15-30°C (59-86°F). (See USP Controlled Room Temperature.)

17 PATIENT COUNSELING INFORMATION

Advise patients to take TOPROL-XL regularly and continuously, as directed, preferably with or immediately following meals. If a dose is missed, the patient should take only the next scheduled dose (without doubling it). Patients should not interrupt or discontinue TOPROL-XL without consulting the physician.

Advise patients (1) to avoid operating automobiles and machinery or engaging in other tasks requiring alertness until the patient’s response to therapy with TOPROL-XL has been determined; (2) to contact the physician if any difficulty in breathing occurs; (3) to inform the physician or dentist before any type of surgery that he or she is taking TOPROL-XL.

Heart failure patients should be advised to consult their physician if they experience signs or symptoms of worsening heart failure such as weight gain or increasing shortness of breath.

Risk of hypoglycemia
Inform parents or caregivers of patients that there is a risk of hypoglycemia when TOPROL-XL is given to patients who are not feeding regularly or who are vomiting. Instruct parents or caregivers how to recognize the signs of hypoglycemia. Monitor for signs and symptoms of hypoglycemia in patients [see Warnings and Precautions (5.7)].

TOPROL-XL® and PLENDIL are trademarks of the AstraZeneca group of companies.

Manufactured by:
AstraZeneca AB
Södertälje, Sweden
Product of Sweden

Manufactured for:

Aralez Pharmaceuticals US Inc.

300 Interpace Parkway
Morris Corporate Center 1, Building C3
Parsippany, NJ 07054

Rev. 04/2023

PACKAGE/LABEL PRINCIPAL DISPLAY PANEL – 25 MG

NDC 70347-025-02

100 tablets

TOPROL-XL®

(metoprolol succinate)

extended-release tablets

25 mg*

Rx only

CAUTION Verify Product Dispensed

Aralez Pharmaceuticals US Inc.

NDC 70347-025-03

1000 tablets

TOPROL-XL®

(metoprolol succinate)

extended-release tablets

25 mg*

Rx only

CAUTION Verify Product Dispensed

Aralez Pharmaceuticals US Inc.

PACKAGE/LABEL PRINCIPAL DISPLAY PANEL – 50 mg

NDC 70347-050-02

100 tablets

TOPROL-XL®

(metoprolol succinate)

extended-release tablets

50 mg*

Rx only

CAUTION Verify Product Dispensed

Aralez Pharmaceuticals US Inc.

NDC 70347-050-03

1000 tablets

TOPROL-XL®

(metoprolol succinate)

extended-release tablets

50 mg*

Rx only

CAUTION Verify Product Dispensed

Aralez Pharmaceuticals US Inc.

PACKAGE/LABEL PRINCIPAL DISPLAY PANEL – 100 mg

NDC 70347-100-02

100 tablets

TOPROL-XL®

(metoprolol succinate)

extended-release tablets

100 mg*

Rx only

CAUTION Verify Product Dispensed

Aralez Pharmaceuticals US Inc.

NDC 70347-100-03

1000 tablets

TOPROL-XL®

(metoprolol succinate)

extended-release tablets

100 mg*

Rx only

CAUTION Verify Product Dispensed

AAralez Pharmaceuticals US Inc.

PACKAGE/LABEL PRINCIPAL DISPLAY PANEL – 200 mg

NDC 70347-200-02

100 tablets

TOPROL-XL®

(metoprolol succinate)

extended-release tablets

200 mg*

Rx only

CAUTION Verify Product Dispensed

Aralez Pharmaceuticals US Inc.

NDC 70347-200-03

1000 tablets

TOPROL-XL®

(metoprolol succinate)

extended-release tablets

200 mg*

Rx only

CAUTION Verify Product Dispensed

Aralez Pharmaceuticals US Inc.